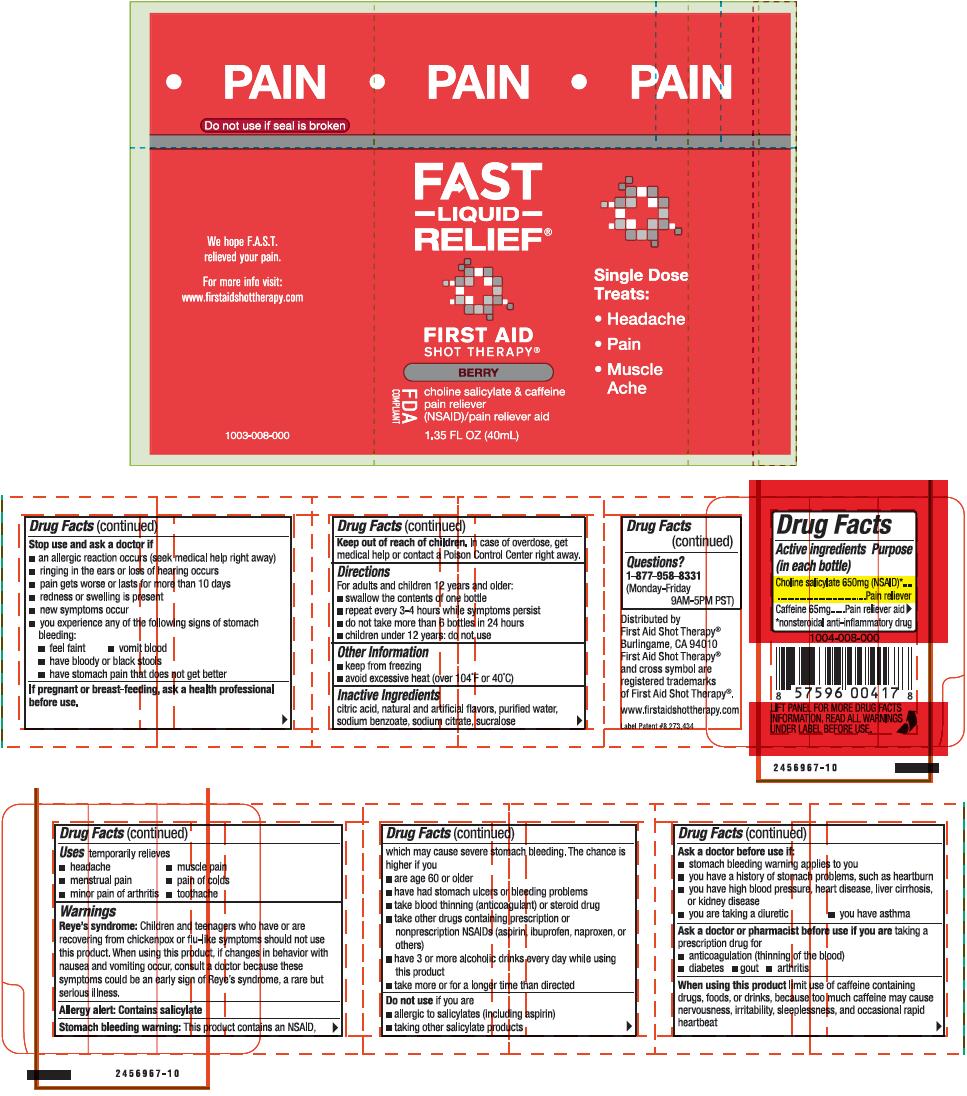 DRUG LABEL: First Aid Shot Therapy Pain Relief
NDC: 57815-081 | Form: LIQUID
Manufacturer: First Aid Beverages, Inc.
Category: otc | Type: HUMAN OTC DRUG LABEL
Date: 20150121

ACTIVE INGREDIENTS: Choline Salicylate 650 mg/40 mL; Caffeine 65 mg/40 mL
INACTIVE INGREDIENTS: Anhydrous Citric Acid; Sodium Benzoate; Sodium Citrate; Sucralose; Water

First Aid Shot Therapy® Pain Relief

Drug Facts

ACTIVE INGREDIENT

PURPOSE

Active ingredients | Purposes
Choline salicylate 650 mg (NSAID) [nonsteroidal anti-inflammatory drug] | Pain reliever
Caffeine 65 mg | Pain reliever aid

Uses

- headache
- muscle pain
- toothache
- menstrual pain
- pain of colds
- minor pain of arthritis

Warnings

Reye's syndrome

Children and teenagers who have or are recovering from chickenpox or flu-like symptoms should not use this product. When using this product, if changes in behavior with nausea and vomiting occur, consult a doctor because these symptoms could be an early sign of Reye's syndrome, a rare but serious illness.

Allergy alert: contains salicylate

Stomach bleeding warning

This product contains an NSAID, which may cause severe stomach bleeding. The chance is higher if you:

- are age 60 or older
- have had stomach ulcers or bleeding problems
- take blood thinning (anticoagulant) or steroid drug
- take other drugs containing prescription or nonprescription NSAIDs (aspirin, ibuprofen, naproxen, or others)
- have 3 or more alcoholic drinks every day while using this product
- take more or for a longer time than directed

Do not use if you are

- allergic to salicylates (including aspirin)
- taking other salicylate products

Ask a doctor before use if

- stomach bleeding warning applies to you
- you have a history of stomach problems, such as heartburn
- you have high blood pressure, heart disease, liver cirrhosis, or kidney disease
- you are taking a diuretic
- you have asthma

Ask a doctor or pharmacist before use if you are taking a prescription drug for

- anticoagulation (thinning of the blood)
- diabetes
- gout
- arthritis

When using this product limit use of caffeine containing drugs, foods, or drinks, because too much caffeine may cause nervousness, irritability, sleeplessness, and occasional rapid heartbeat

Stop use and ask a doctor if

- an allergic reaction occurs (seek medical help right away)
- ringing in the ears or loss of hearing occurs
- pain gets worse or lasts for more than 10 days
- redness or swelling is present
- new symptoms occur
- you experience any of the following signs of stomach bleeding:
  - feel faint
  - vomit blood
  - have bloody or black stools
  - have stomach pain that does not get better

PREGNANCY OR BREAST FEEDING

If pregnant or breast-feeding, ask a health professional before use.

Keep out of reach of children. In case of overdose, get medical help or contact a Poison Control Center right away.

Directions

- Adults and children 12 years and over:
  - swallow the contents of one bottle
  - repeat every 3-4 hours while symptoms persist
  - do not take more than 6 bottles in 24 hours
- Children under 12 years: Do not use

Other information

- keep from freezing
- avoid excessive heat (over 104°F or 40°C)

Inactive ingredients

Citric acid, natural and artificial flavors, purified water, sodium benzoate, sodium citrate, sucralose

Questions or comments?

1-877-958-8331 (Monday-Friday 9AM-5PM PST). You may also report serious side effects to this number.

Distributed by
First Aid Shot Therapy®
Burlingame, CA 94010

PRINCIPAL DISPLAY PANEL - 40 mL Bottle Label

●
PAIN

FAST
– LIQUID –
RELIEF®

FIRST AID
SHOT THERAPY®

BERRY

FDA
COMPLIANT

choline salicylate & caffeine
pain reliever
(NSAID)/pain reliever aid

1.35 FL OZ (40mL)